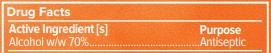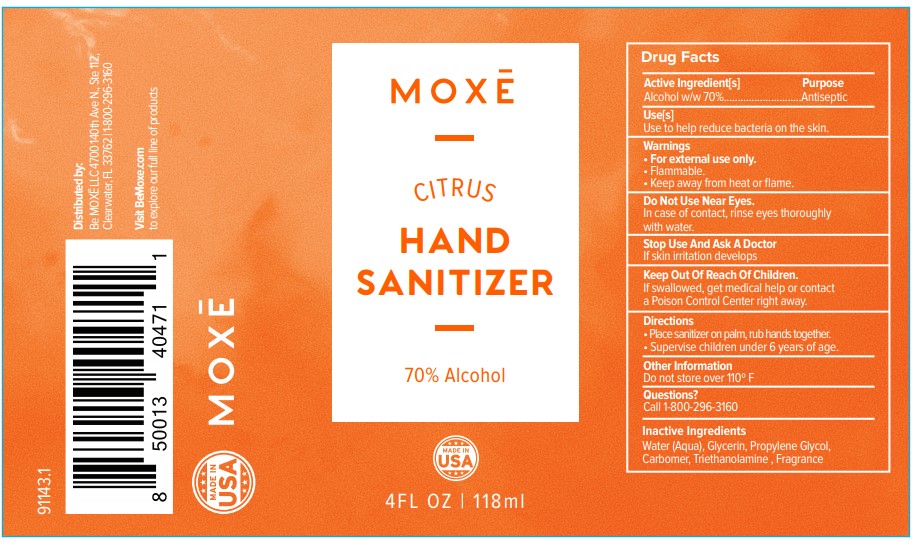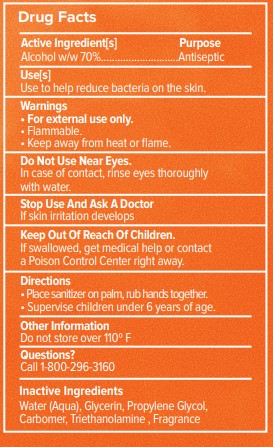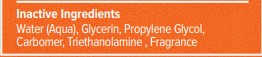 DRUG LABEL: Moxe
NDC: 73333-059 | Form: GEL
Manufacturer: Nutrix International, LLC.
Category: otc | Type: HUMAN OTC DRUG LABEL
Date: 20200509

ACTIVE INGREDIENTS: ALCOHOL 0.7 g/59 g
INACTIVE INGREDIENTS: TANGERINE 0.005 g/59 g; PROPYLENE GLYCOL 0.015 g/59 g; TROLAMINE 0.0012 g/59 g; WATER 0.2598 g/59 g; GLYCERIN 0.015 g/59 g; CARBOMER 940 0.004 g/59 g

Active Ingredient[s

Alcohol 70%

Use[s]

Use to help reduce bacteria on the skin.

Warnings

• For external use only.

• Flammable.

• Keep away from heat or flame.

Do not use near eyes In case of contact, rinse eyes thoroughly with water

Stop Use

Stop Use And Ask A Doctor If skin irritation develops.

Purpose

Antiseptic

Directions

• Place sanitizer on palm, rub hands together.

• Supervise children under 6 years of age.

Keep out of reach of children

If swallowed, get medical help or contact a Poison Control Center right away.

Other Information

Do not store over 110º F

Inactive Ingredients

Water (Aqua), Glycerin, Propylene Glycol, Carbomer, Triethanolamine , Fragrance